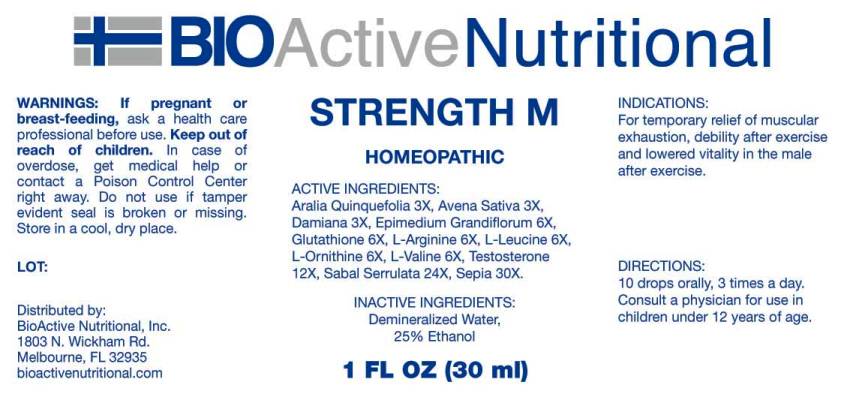 DRUG LABEL: Strength M
NDC: 43857-0428 | Form: LIQUID
Manufacturer: BioActive Nutritional, Inc.
Category: homeopathic | Type: HUMAN OTC DRUG LABEL
Date: 20241018
DEA Schedule: CIII

ACTIVE INGREDIENTS: AMERICAN GINSENG 3 [hp_X]/1 mL; AVENA SATIVA FLOWERING TOP 3 [hp_X]/1 mL; TURNERA DIFFUSA LEAFY TWIG 3 [hp_X]/1 mL; EPIMEDIUM GRANDIFLORUM TOP 6 [hp_X]/1 mL; GLUTATHIONE 6 [hp_X]/1 mL; ARGININE 6 [hp_X]/1 mL; LEUCINE 6 [hp_X]/1 mL; ORNITHINE 6 [hp_X]/1 mL; VALINE 6 [hp_X]/1 mL; TESTOSTERONE 12 [hp_X]/1 mL; SAW PALMETTO 24 [hp_X]/1 mL; SEPIA OFFICINALIS JUICE 30 [hp_X]/1 mL
INACTIVE INGREDIENTS: WATER; ALCOHOL

DRUG FACTS:

ACTIVE INGREDIENTS:

Aralia Quinquefolia 3X, Avena Sativa 3X, Damiana 3X, Epimedium Grandiflorum 6X, Glutathione 6X, L-Arginine 6X, L-Leucine 6X, L-Ornithine 6X, L-Valine 6X, Testosterone 12X, Sabal Serrulata 24X, Sepia 30X.

INDICATIONS:

For temporary relief of muscular exhaustion, debility after exercise and lowered vitality in the male after exercise.

WARNINGS:

If pregnant or breast-feeding, ask a health care professional before use.

Keep out of reach of children. In case of overdose, get medical help or contact a Poison Control Center right away.

Do not use if tamper evident seal is broken or missing.

Store in cool, dry place.

Keep out of reach of children. In case of overdose, get medical help or contact a Poison Control Center right away.

DIRECTIONS:

10 drops orally, 3 times a day. Consult a physician for use in children under 12 years of age.

INDICAITONS:

For temporary relief of muscular exhaustion, debility after exercise and lowered vitality in the male after exercise.

INACTIVE INGREDIENTS:

Demineralized Water, 25% Ethanol

QUESTIONS:

Distributed by:
BioActive Nutritional, Inc.
1803 N. Wickham Rd.
Melbourne, FL 32935
bioactivenutritional.com

PACKAGE LABEL DISPLAY:

BIOActive Nutritional

STRENGTH M

HOMEOPATHIC

1 FL OZ (30 ml)